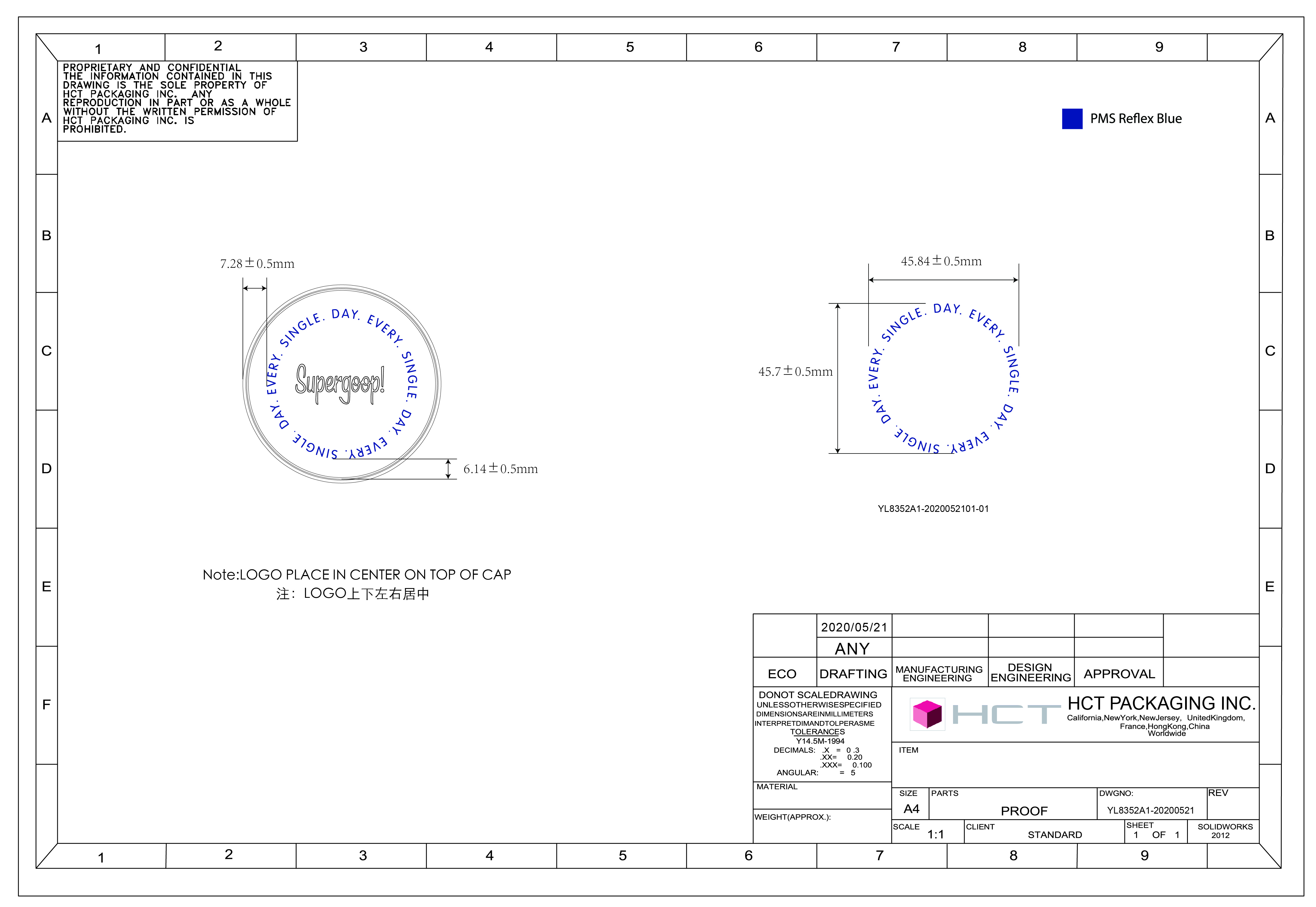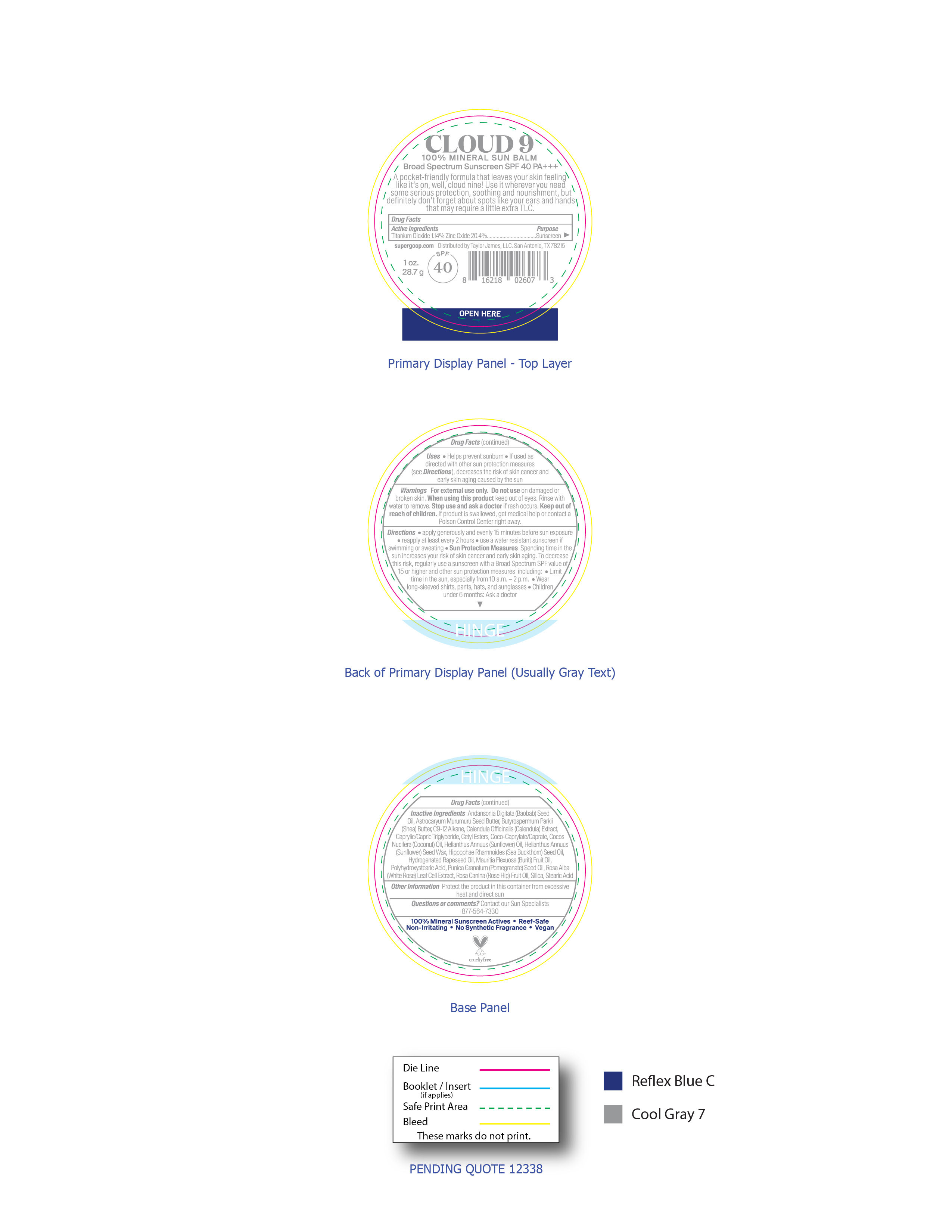 DRUG LABEL: Cloud 9 100% Mineral Sun Balm Broad Spectrum Sunscreen SPF 40
NDC: 75936-512 | Form: CREAM
Manufacturer: Supergoop, LLC
Category: otc | Type: HUMAN OTC DRUG LABEL
Date: 20240102

ACTIVE INGREDIENTS: TITANIUM DIOXIDE 1.14 g/100 g; ZINC OXIDE 20.4 g/100 g
INACTIVE INGREDIENTS: 1,3-BUTYLENE GLYCOL 1-STEARATE; HIPPOPHAE RHAMNOIDES FRUIT OIL; HELIANTHUS ANNUUS SEED WAX; HYDROGENATED RAPESEED OIL; POLYHYDROXYSTEARIC ACID (2300 MW); SHEA BUTTER; MAURITIA FLEXUOSA FRUIT OIL; ASTROCARYUM MURUMURU SEED BUTTER; CALENDULA OFFICINALIS FLOWER; PUNICA GRANATUM SEED OIL; CETYL ESTERS WAX; COCO-CAPRYLATE/CAPRATE; SUNFLOWER OIL; ADANSONIA DIGITATA SEED OIL; COCONUT OIL; ROSA CANINA FRUIT OIL; SILICON DIOXIDE; MEDIUM-CHAIN TRIGLYCERIDES

Cloud 9 100% Mineral Sun Balm Broad Spectrum Sunscreen SPF 40

Active Ingredients

Titanium Dioxide 1.14%, Zinc Oxide 20.4% Purpose Sunscreen

Uses

Helps prevent sunburn. If used as directed with other sun protection measures (see Directions), decreases the risk of skin cancer and early skin aging caused by the sun.

Keep out of reach of children. If product is swallowed, get medical help or contact Poison Control Center right away.

Stop use and ask a doctor if rash occurs.

Warnings

For external use only. Do not use on damaged or broken skin. When using the product keep out of eyes. Rinse with water to remove. Stop use and ask a doctor if rash occurs. Keep out of reach of children. If product is swallowed, get medical help or contact Poison Control Center right away.

Directions

- Apply generously and evenly 15 minutes before sun exposure
- reapply at least every 2 hours
- use a water resistant sunscreen if swimming or sweating
- Sun Protection Measures Spending time in the sun increases your risk of skin cancer and early skin aging.
- To decrease this risk, regularly use a sunscreen with a Broad Spectrum SPF value of 15 or higher and other sun protection measures including: limit time in the sun especially from 10 a.m.- 2 p.m. Wear long-sleeved shirts, pants, hats, and sunglasses.
- Children under 6 months: Ask a doctor

Inactive Ingredients

Adansonia Digitata (Baobab) Seed Oil, Astrocaryum Murumuru Seed Butter, Butyrospermum Parkii (Shea) Butter, C9-12 Alkane, Calendula Officinalis (Calendula) Extract, Caprylic/Capric Triglyceride, Cetyl Esters, Coco-Caprylate/Caprate, Cocos Nucifera (Coconut) Oil, Helianthus Annuus (Sunflower) Oil, Helianthus Annuus (Sunflower) Seed Wax, Hippophae Rhamnoides (Sea Buckthorn) Seed Oil, Hydrogenated Rapeseed Oil, Mauritia Flexuosa (Buriti) Fruit Oil, Polyhydroxystearic Acid, Punica Granatum (Pomegranate) Seed Oil, Rosa Alba (White Rose) Leaf Cell Extract, Rosa Canina (Rose Hip) Fruit Oil, Silica, Stearic Acid

OTHER SAFETY INFORMATION

Protect the product in this container from excessive heat and direct sun

Questions or commnets? Contact our Sun Specialists 877-564-7330

Stop use and ask a doctor if rash occurs

PACKAGE LABEL

CLOUD 9

100% MINERAL SUN BALM

Broad Spectrum Sunscreen SPF 40 PA+++

Cloud 9 100% Mineral Sun Balm SPF 40 is a pocket-friendly formula that leaves your skin feeling like it's on, well, cloud nine. Use it wherever you need some serious protection, soothing and nourishment, but definitely don't forget about spots like your ears and hands that may require little extra TLC.

supergoop.com Distributed by Taylor James, LLC. San Antonio, TX 78215

SPF 40

Cruelty free

1 oz./28.7g

100% Mineral Sunscreen Actives. Reef-Safe. Non-Irritating. No Synthetic Fragrance. Vegan.